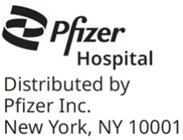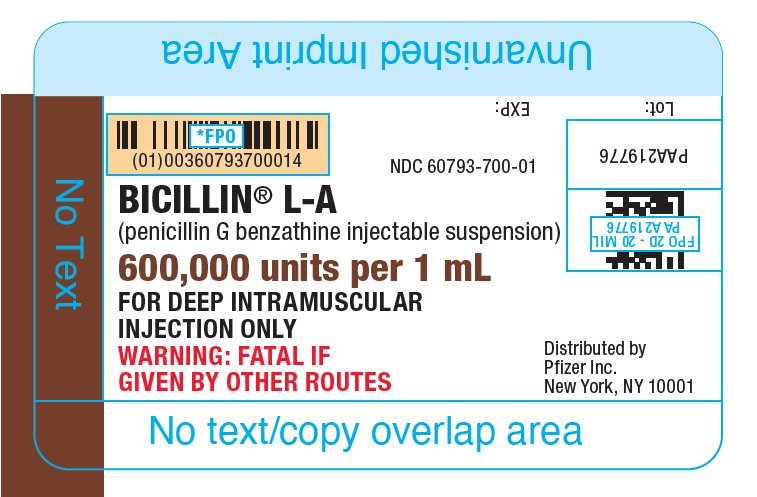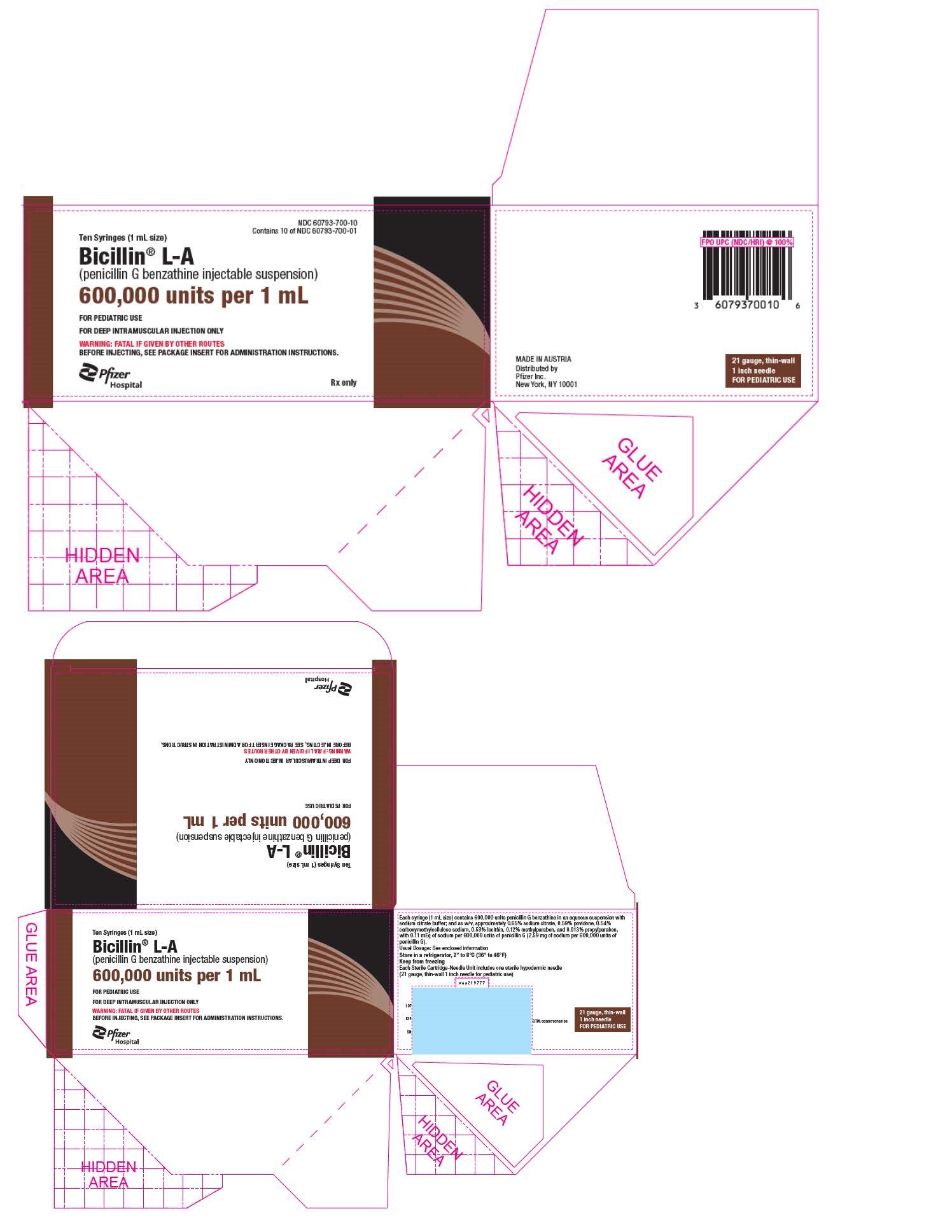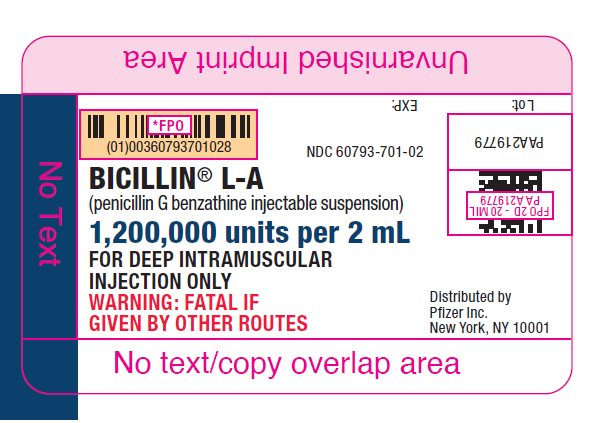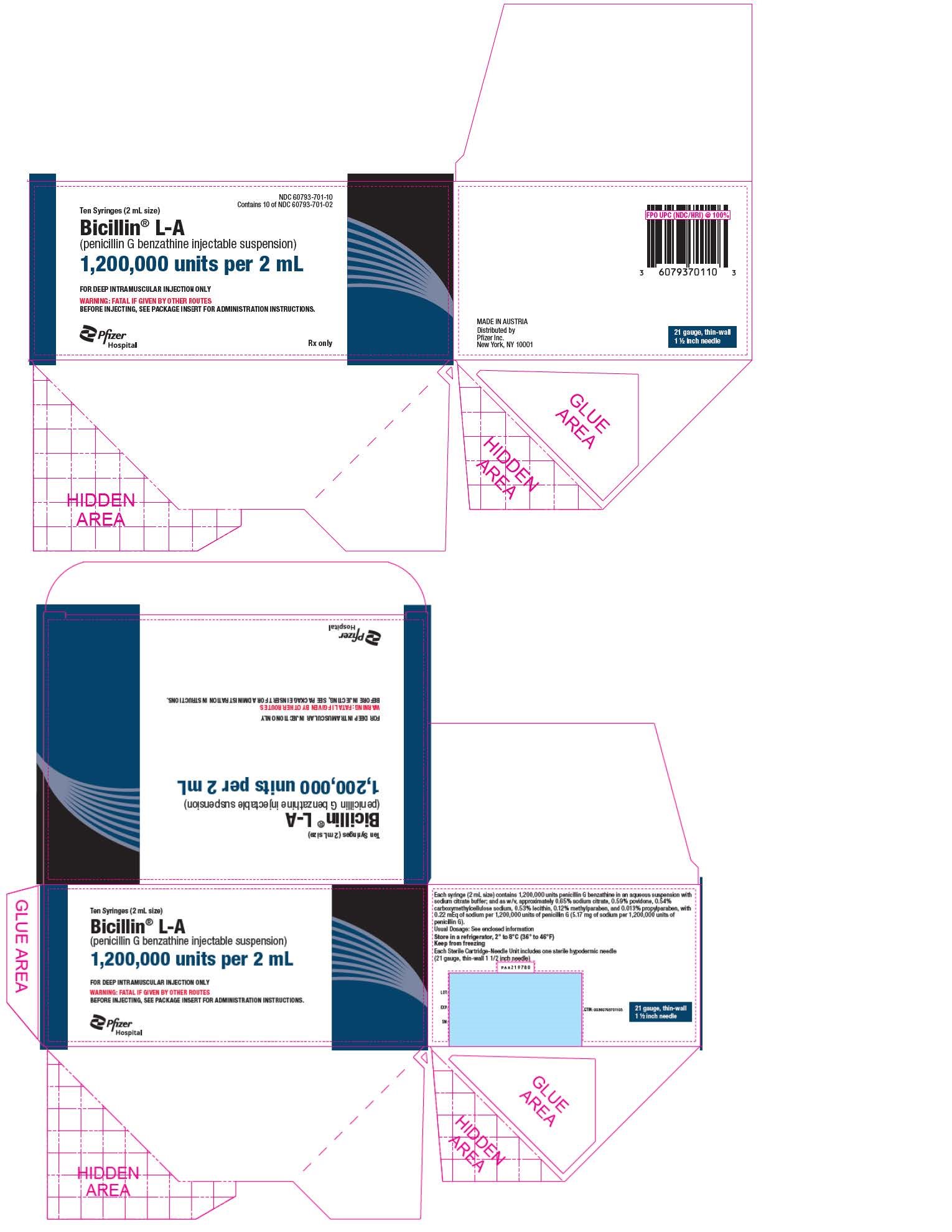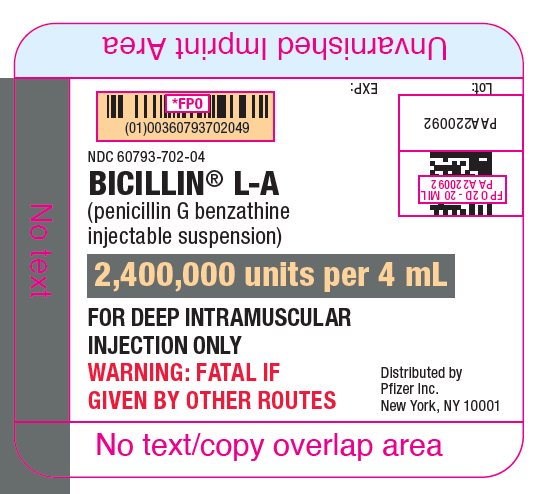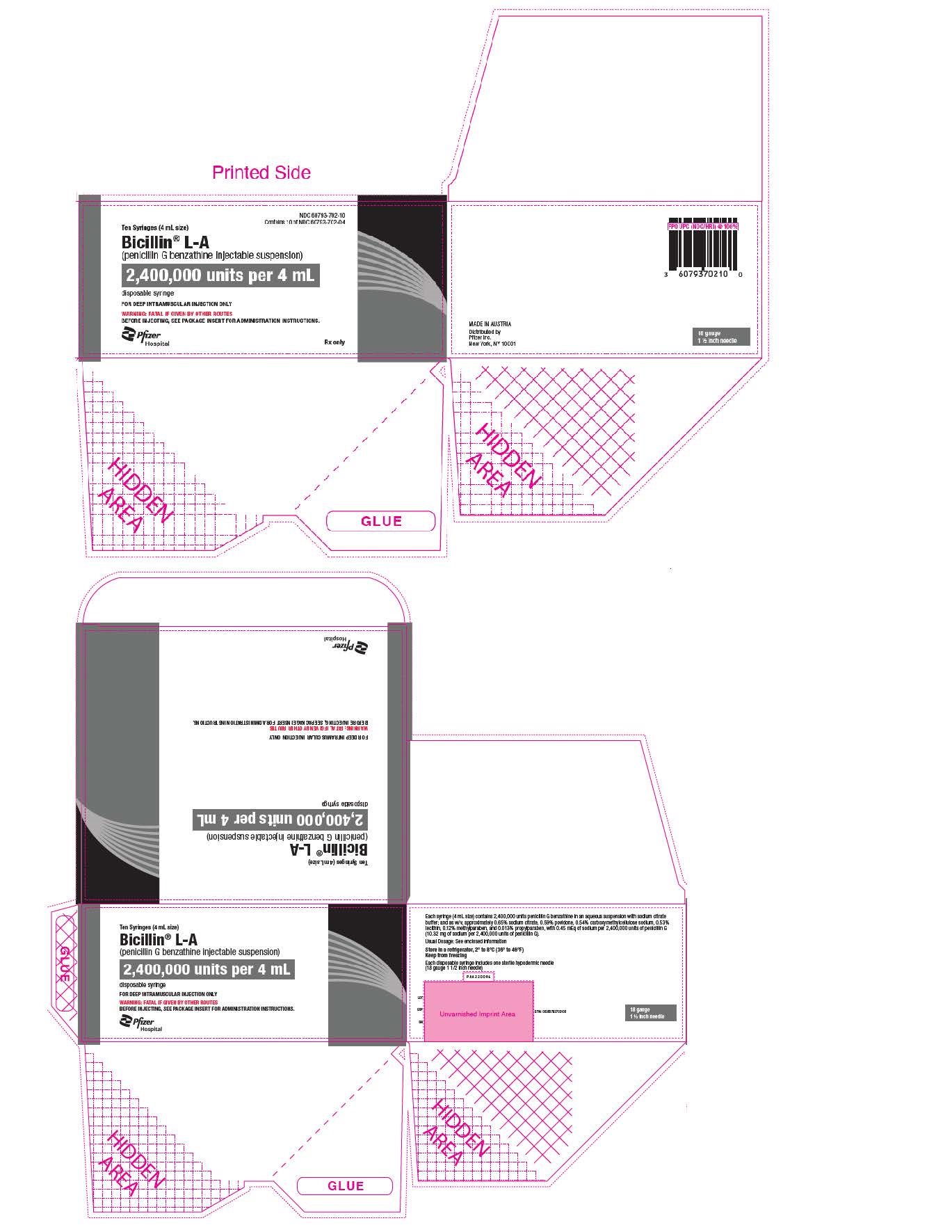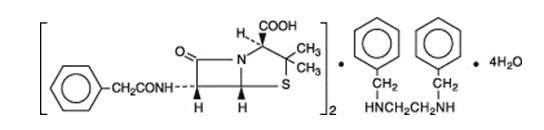 DRUG LABEL: BICILLIN L-A
NDC: 60793-700 | Form: INJECTION, SUSPENSION
Manufacturer: Pfizer Laboratories Div Pfizer Inc
Category: prescription | Type: HUMAN PRESCRIPTION DRUG LABEL
Date: 20240712

ACTIVE INGREDIENTS: PENICILLIN G BENZATHINE 600000 [iU]/1 mL
INACTIVE INGREDIENTS: LECITHIN, SOYBEAN; CARBOXYMETHYLCELLULOSE SODIUM, UNSPECIFIED; POVIDONE, UNSPECIFIED; METHYLPARABEN; PROPYLPARABEN; SODIUM CITRATE, UNSPECIFIED FORM; WATER

Bicillin® L-A
(penicillin G benzathine injectable suspension)
Disposable Syringe

For deep IM injection only.

WARNING

NOT FOR INTRAVENOUS USE. DO NOT INJECT INTRAVENOUSLY OR ADMIX WITH OTHER INTRAVENOUS SOLUTIONS. THERE HAVE BEEN REPORTS OF INADVERTENT INTRAVENOUS ADMINISTRATION OF PENICILLIN G BENZATHINE WHICH HAS BEEN ASSOCIATED WITH CARDIORESPIRATORY ARREST AND DEATH. Prior to administration of this drug, carefully read the WARNINGS, ADVERSE REACTIONS, and DOSAGE AND ADMINISTRATION sections of the labeling.

To reduce the development of drug-resistant bacteria and maintain the effectiveness of Bicillin L-A and other antibacterial drugs, Bicillin L-A should be used only to treat or prevent infections that are proven or strongly suspected to be caused by bacteria.

Description

Bicillin L-A (penicillin G benzathine injectable suspension) is available for deep intramuscular injection. Penicillin G benzathine is prepared by the reaction of dibenzylethylene diamine with two molecules of penicillin G. It is chemically designated as (2S, 5R, 6R)-3,3-Dimethyl-7-oxo-6-(2-phenylacetamido)-4-thia-1-azabicyclo[3.2.0]heptane-2-carboxylic acid compound with N,N' -dibenzylethylenediamine (2:1), tetrahydrate. It occurs as a white, crystalline powder and is very slightly soluble in water and sparingly soluble in alcohol. Its chemical structure is as follows:

Bicillin L-A contains penicillin G benzathine in aqueous suspension with sodium citrate buffer and, as w/v, approximately 0.65% sodium citrate, 0.59% povidone, 0.54% carboxymethylcellulose sodium, 0.53% lecithin, 0.12% methylparaben, and 0.013% propylparaben.

Bicillin L-A contains approximately 0.11 mEq of sodium per 600,000 units of penicillin G (approximately 2.59 mg of sodium per 600,000 units of penicillin G).

Bicillin L-A suspension in the disposable-syringe formulation is viscous and opaque. It is available in a 1 mL, 2 mL, and 4 mL sizes containing the equivalent of 600,000 (actual volume of 1.17 mL contains 620,100), 1,200,000 (actual volume of 2.34 mL contains 1,240,200), and 2,400,000 (actual volume of 4.67 mL contains 2,475,100) units respectively of penicillin G as the benzathine salt. Read CONTRAINDICATIONS, WARNINGS, PRECAUTIONS, and DOSAGE AND ADMINISTRATION sections prior to use.

CLINICAL PHARMACOLOGY

General

Penicillin G benzathine has an extremely low solubility and, thus, the drug is slowly released from intramuscular injection sites. The drug is hydrolyzed to penicillin G. This combination of hydrolysis and slow absorption results in blood serum levels much lower but much more prolonged than other parenteral penicillins.

Intramuscular administration of 300,000 units of penicillin G benzathine in adults results in blood levels of 0.03 to 0.05 units per mL, which are maintained for 4 to 5 days. Similar blood levels may persist for 10 days following administration of 600,000 units and for 14 days following administration of 1,200,000 units. Blood concentrations of 0.003 units per mL may still be detectable 4 weeks following administration of 1,200,000 units.

Approximately 60% of penicillin G is bound to serum protein. The drug is distributed throughout the body tissues in widely varying amounts. Highest levels are found in the kidneys with lesser amounts in the liver, skin, and intestines. Penicillin G penetrates into all other tissues and the spinal fluid to a lesser degree. With normal kidney function, the drug is excreted rapidly by tubular excretion. In neonates and young infants and in individuals with impaired kidney function, excretion is considerably delayed.

Microbiology

Mechanism of Action

Penicillin G exerts a bactericidal action against penicillin-susceptible microorganisms during the stage of active multiplication. It acts through the inhibition of biosynthesis of cell-wall peptidoglycan, rendering the cell wall osmotically unstable.

Resistance

Penicillin is not active against penicillinase-producing bacteria or against organisms resistant to beta-lactams because of alterations in the penicillin-binding proteins. Resistance to penicillin G has not been reported in Streptococcus pyogenes.

Antimicrobial Activity

Penicillin has been shown to be active against most isolates of the following bacteria, both in vitro and in clinical infections as described in the INDICATIONS AND USAGE section.

Gram-positive bacteria

Beta-hemolytic streptococci (groups A, B, C, G, H, L and M).

Other microorganisms
Treponema pallidum
Treponema carateum

Susceptibility Testing

For specific information regarding susceptibility test interpretive criteria and associated test methods and quality control standards recognized by FDA for this drug, please see: https://www.fda.gov/STIC.

INDICATIONS AND USAGE

To reduce the development of drug-resistant bacteria and maintain the effectiveness of Bicillin L-A and other antibacterial drugs, Bicillin L-A should be used only to treat or prevent infections that are proven or strongly suspected to be caused by bacteria. When culture and susceptibility information are available, they should be considered in selecting or modifying antibacterial therapy. In the absence of such data, local epidemiology and susceptibility patterns may contribute to the empiric selection of therapy.

Intramuscular penicillin G benzathine is indicated in the treatment of infections due to penicillin-G-sensitive microorganisms that are susceptible to the low and very prolonged serum levels common to this particular dosage form. Therapy should be guided by bacteriological studies (including sensitivity tests) and by clinical response.

The following infections will usually respond to adequate dosage of intramuscular penicillin G benzathine:

Mild-to-moderate infections of the upper-respiratory tract due to susceptible streptococci.

Venereal infections—Syphilis, yaws, bejel, and pinta.

Medical Conditions in which Penicillin G Benzathine Therapy is indicated as Prophylaxis:

Rheumatic fever and/or chorea—Prophylaxis with penicillin G benzathine has proven effective in preventing recurrence of these conditions. It has also been used as follow-up prophylactic therapy for rheumatic heart disease and acute glomerulonephritis.

CONTRAINDICATIONS

A history of a previous hypersensitivity reaction to any of the penicillins is a contraindication.

WARNINGS

WARNING

NOT FOR INTRAVENOUS USE. DO NOT INJECT INTRAVENOUSLY OR ADMIX WITH OTHER INTRAVENOUS SOLUTIONS. THERE HAVE BEEN REPORTS OF INADVERTENT INTRAVENOUS ADMINISTRATION OF PENICILLIN G BENZATHINE WHICH HAS BEEN ASSOCIATED WITH CARDIORESPIRATORY ARREST AND DEATH. Prior to administration of this drug, carefully read the WARNINGS, ADVERSE REACTIONS, and DOSAGE AND ADMINISTRATION sections of the labeling.

Penicillin G benzathine should only be prescribed for the indications listed in this insert.

Anaphylaxis

SERIOUS AND OCCASIONALLY FATAL HYPERSENSITIVITY (ANAPHYLACTIC) REACTIONS HAVE BEEN REPORTED IN PATIENTS ON PENICILLIN THERAPY. THESE REACTIONS ARE MORE LIKELY TO OCCUR IN INDIVIDUALS WITH A HISTORY OF PENICILLIN HYPERSENSITIVITY AND/OR A HISTORY OF SENSITIVITY TO MULTIPLE ALLERGENS. THERE HAVE BEEN REPORTS OF INDIVIDUALS WITH A HISTORY OF PENICILLIN HYPERSENSITIVITY WHO HAVE EXPERIENCED SEVERE REACTIONS WHEN TREATED WITH CEPHALOSPORINS. BEFORE INITIATING THERAPY WITH BICILLIN L-A, CAREFUL INQUIRY SHOULD BE MADE CONCERNING PREVIOUS HYPERSENSITIVITY REACTIONS TO PENICILLINS, CEPHALOSPORINS, OR OTHER ALLERGENS. IF AN ALLERGIC REACTION OCCURS, BICILLIN L-A SHOULD BE DISCONTINUED AND APPROPRIATE THERAPY INSTITUTED. SERIOUS ANAPHYLACTIC REACTIONS REQUIRE IMMEDIATE EMERGENCY TREATMENT WITH EPINEPHRINE. OXYGEN, INTRAVENOUS STEROIDS AND AIRWAY MANAGEMENT, INCLUDING INTUBATION, SHOULD ALSO BE ADMINISTERED AS INDICATED.

Severe cutaneous adverse reactions (SCAR), such as Stevens-Johnson syndrome (SJS), toxic epidermal necrolysis (TEN), drug reaction with eosinophilia and systemic symptoms (DRESS), and acute generalized exanthematous pustulosis (AGEP) have been reported in patients taking penicillin G (the active moiety in Bicillin L-A). When SCAR is suspected, Bicillin L-A should be discontinued immediately and an alternative treatment should be considered.

Clostridioides difficile associated-diarrhea (CDAD) has been reported with use of nearly all antibacterial agents, including Bicillin L-A, and may range in severity from mild diarrhea to fatal colitis. Treatment with antibacterial agents alters the normal flora of the colon leading to overgrowth of C. difficile.

C. difficile produces toxins A and B which contribute to the development of CDAD. Hypertoxin producing strains of C. difficile cause increased morbidity and mortality, as these infections can be refractory to antimicrobial therapy and may require colectomy. CDAD must be considered in all patients who present with diarrhea following antibacterial use. Careful medical history is necessary since CDAD has been reported to occur over two months after the administration of antibacterial agents.

If CDAD is suspected or confirmed, ongoing antibiotic use not directed against C. difficile may need to be discontinued. Appropriate fluid and electrolyte management, protein supplementation, antibiotic treatment of C. difficile, and surgical evaluation should be instituted as clinically indicated.

Method of Administration

Do not inject into or near an artery or nerve. See administration instructions below.

Injection into or near a nerve may result in permanent neurological damage.

Inadvertent intravascular administration, including inadvertent direct intra-arterial injection or injection immediately adjacent to arteries, of Bicillin L-A and other penicillin preparations has resulted in severe neurovascular damage, including transverse myelitis with permanent paralysis, gangrene requiring amputation of digits and more proximal portions of extremities, and necrosis and sloughing at and surrounding the injection site consistent with the diagnosis of Nicolau syndrome. Such severe effects have been reported following injections into the buttock, thigh, and deltoid areas. Other serious complications of suspected intravascular administration which have been reported include immediate pallor, mottling, or cyanosis of the extremity both distal and proximal to the injection site, followed by bleb formation; severe edema requiring anterior and/or posterior compartment fasciotomy in the lower extremity. The above-described severe effects and complications have most often occurred in infants and small children. Prompt consultation with an appropriate specialist is indicated if any evidence of compromise of the blood supply occurs at, proximal to, or distal to the site of injection.^1–9 (See PRECAUTIONS, and DOSAGE AND ADMINISTRATION sections.)

FOR DEEP INTRAMUSCULAR INJECTION ONLY. There have been reports of inadvertent intravenous administration of penicillin G benzathine which has been associated with cardiorespiratory arrest and death. Therefore, do not inject intravenously or admix with other intravenous solutions. (See DOSAGE AND ADMINISTRATION section.)

Administer by DEEP INTRAMUSCULAR INJECTION ONLY in the upper, outer quadrant of the buttock (dorsogluteal) or the ventrogluteal site. Quadriceps femoris fibrosis and atrophy have been reported following repeated intramuscular injections of penicillin preparations into the anterolateral thigh. Because of these adverse effects and the vascularity of this region, administration in the anterolateral thigh is not recommended.

PRECAUTIONS

General

Prescribing Bicillin L-A in the absence of a proven or strongly suspected bacterial infection or a prophylactic indication is unlikely to provide benefit to the patient and increases the risk of a development of drug-resistant bacteria.

Penicillin should be used with caution in individuals with histories of significant allergies and/or asthma.

Care should be taken to avoid intravenous or intra-arterial administration, or injection into or near major peripheral nerves or blood vessels, since such injection may produce neurovascular damage. (See WARNINGS, and DOSAGE AND ADMINISTRATION sections.)

Prolonged use of antibiotics may promote the overgrowth of nonsusceptible organisms, including fungi. Should superinfection occur, appropriate measures should be taken.

Bicillin L-A contains approximately 0.11 mEq of sodium per 600,000 units of penicillin G (approximately 2.59 mg of sodium per 600,000 units of penicillin G).

Information for Patients

Diarrhea is a common problem caused by antibiotics which usually ends when the antibiotic is discontinued. Sometimes after starting treatment with antibiotics, patients can develop watery and bloody stools (with or without stomach cramps and fever) even as late as two or more months after having taken the last dose of the antibiotic. If this occurs, patients should contact their physician as soon as possible.

Patients should be counseled that antibacterial drugs including Bicillin L-A should only be used to treat bacterial infections. They do not treat viral infections (e.g., the common cold). When Bicillin L-A is prescribed to treat a bacterial infection, patients should be told that although it is common to feel better early in the course of therapy, the medication should be taken exactly as directed. Skipping doses or not completing the full course of therapy may (1) decrease the effectiveness of the immediate treatment and (2) increase the likelihood that bacteria will develop resistance and will not be treatable by Bicillin L-A or other antibacterial drugs in the future.

Laboratory Tests

In streptococcal infections, therapy must be sufficient to eliminate the organism; otherwise, the sequelae of streptococcal disease may occur. Cultures should be taken following completion of treatment to determine whether streptococci have been eradicated.

Drug Interactions

Tetracycline, a bacteriostatic antibiotic, may antagonize the bactericidal effect of penicillin, and concurrent use of these drugs should be avoided.

Concurrent administration of penicillin and probenecid increases and prolongs serum penicillin levels by decreasing the apparent volume of distribution and slowing the rate of excretion by competitively inhibiting renal tubular secretion of penicillin.

Pregnancy

Teratogenic effects

Pregnancy Reproduction studies performed in the mouse, rat, and rabbit have revealed no evidence of impaired fertility or harm to the fetus due to penicillin G. Human experience with the penicillins during pregnancy has not shown any positive evidence of adverse effects on the fetus. There are, however, no adequate and well-controlled studies in pregnant women showing conclusively that harmful effects of these drugs on the fetus can be excluded. Because animal reproduction studies are not always predictive of human response, this drug should be used during pregnancy only if clearly needed.

Nursing Mothers

Soluble penicillin G (the hydrolysate of penicillin G benzathine) is excreted in breast milk. Caution should be exercised when penicillin G benzathine is administered to a nursing woman.

Carcinogenesis, Mutagenesis, Impairment of Fertility

No long-term animal studies have been conducted with this drug.

Pediatric Use

(See INDICATIONS AND USAGE and DOSAGE AND ADMINISTRATION sections.)

Geriatric Use

Clinical studies of penicillin G benzathine did not include sufficient numbers of subjects aged 65 and over to determine whether they respond differently from younger subjects. Other reported clinical experience has not identified differences in responses between the elderly and younger patients. In general, dose selection for an elderly patient should be cautious, usually starting at the low end of the dosing range, reflecting the greater frequency of decreased hepatic, renal, or cardiac function, and of concomitant disease or other drug therapy. This drug is known to be substantially excreted by the kidney, and the risk of toxic reactions to this drug may be greater in patients with impaired renal function. (See CLINICAL PHARMACOLOGY.) Because elderly patients are more likely to have decreased renal function, care should be taken in dose selection, and it may be useful to monitor renal function.

ADVERSE REACTIONS

As with other penicillins, untoward reactions of the sensitivity phenomena are likely to occur, particularly in individuals who have previously demonstrated hypersensitivity to penicillins or in those with a history of allergy, asthma, hay fever, or urticaria.

As with other treatments for syphilis, the Jarisch-Herxheimer reaction has been reported.

The following adverse reactions have been reported with Bicillin L-A during post-marketing experience:

Skin and Appendages: Stevens-Johnson syndrome (SJS) and drug reaction with eosinophilia and systemic symptoms (DRESS). (See WARNINGS.)

Immune System Disorders: Acute myocardial ischemia with or without myocardial infarction may occur as part of an allergic reaction (Kounis syndrome).

The following have been reported with parenteral penicillin G (the active moiety in Bicillin L-A):

General: Hypersensitivity reactions including the following: skin eruptions (maculopapular to exfoliative dermatitis), urticaria, laryngeal edema, fever, eosinophilia; other serum sickness-like reactions (including chills, fever, edema, arthralgia, and prostration); and anaphylaxis including shock and death: severe cutaneous adverse reactions (SCAR), such as toxic epidermal necrolysis (TEN) and acute generalized exanthematous pustulosis (AGEP). (See WARNINGS.) Note: Urticaria, other skin rashes, and serum sickness-like reactions may be controlled with antihistamines and, if necessary, systemic corticosteroids. Whenever such reactions occur, penicillin G should be discontinued unless, in the opinion of the physician, the condition being treated is life-threatening and amenable only to therapy with penicillin G. Serious anaphylactic reactions require immediate emergency treatment with epinephrine. Oxygen, intravenous steroids, and airway management, including intubation, should also be administered as indicated.

Gastrointestinal: Pseudomembranous colitis. Onset of pseudomembranous colitis symptoms may occur during or after antibacterial treatment. (See WARNINGS section.)

Hematologic: Hemolytic anemia, leukopenia, thrombocytopenia.

Neurologic: Neuropathy.

Urogenital: Nephropathy.

The following adverse events have been temporally associated with parenteral administration of penicillin G benzathine (a component of Bicillin L-A):

Body as a Whole: Hypersensitivity reactions including allergic vasculitis, pruritus, fatigue, asthenia, and pain; aggravation of existing disorder; headache, Nicolau syndrome.

Cardiovascular: Cardiac arrest; hypotension; tachycardia; palpitations; pulmonary hypertension; pulmonary embolism; vasodilation; vasovagal reaction; cerebrovascular accident; syncope.

Gastrointestinal: Nausea, vomiting; blood in stool; intestinal necrosis.

Hemic and Lymphatic: Lymphadenopathy.

Injection Site: Injection site reactions including pain, inflammation, lump, abscess, necrosis, edema, hemorrhage, cellulitis, hypersensitivity, atrophy, ecchymosis, and skin ulcer. Neurovascular reactions including warmth, vasospasm, pallor, mottling, gangrene, numbness of the extremities, cyanosis of the extremities, and neurovascular damage.

Metabolic: Elevated BUN, creatinine, and SGOT.

Musculoskeletal: Joint disorder; periostitis; exacerbation of arthritis; myoglobinuria; rhabdomyolysis.

Nervous System: Nervousness; tremors; dizziness; somnolence; confusion; anxiety; euphoria; transverse myelitis; seizures; coma. A syndrome manifested by a variety of CNS symptoms such as severe agitation with confusion, visual and auditory hallucinations, and a fear of impending death (Hoigne's syndrome), has been reported after administration of penicillin G procaine and, less commonly, after injection of the combination of penicillin G benzathine and penicillin G procaine. Other symptoms associated with this syndrome, such as psychosis, seizures, dizziness, tinnitus, cyanosis, palpitations, tachycardia, and/or abnormal perception in taste, also may occur.

Respiratory: Hypoxia; apnea; dyspnea.

Skin: Diaphoresis.

Special Senses: Blurred vision; blindness.

Urogenital: Neurogenic bladder; hematuria; proteinuria; renal failure; impotence; priapism.

OVERDOSAGE

Penicillin in overdosage has the potential to cause neuromuscular hyperirritability or convulsive seizures.

DOSAGE AND ADMINISTRATION

Streptococcal (Group A) Upper Respiratory Infections (for example, pharyngitis)

Adults—a single injection of 1,200,000 units; older pediatric patients—a single injection of 900,000 units; infants and pediatric patients under 60 lbs.—300,000 to 600,000 units.

Syphilis

Primary, secondary, and latent—2,400,000 units (1 dose). Late (tertiary and neurosyphilis)—2,400,000 units at 7-day intervals for three doses.

Congenital—under 2 years of age: 50,000 units/kg/body weight; ages 2 to 12 years: adjust dosage based on adult dosage schedule.

Yaws, Bejel, and Pinta—1,200,000 units (1 injection).

Prophylaxis—for rheumatic fever and glomerulonephritis.

Following an acute attack, penicillin G benzathine (parenteral) may be given in doses of 1,200,000 units once a month or 600,000 units every 2 weeks.

METHOD OF ADMINISTRATION

BICILLIN L-A IS INTENDED FOR INTRAMUSCULAR INJECTION ONLY. DO NOT INJECT INTO OR NEAR AN ARTERY OR NERVE, OR INTRAVENOUSLY OR ADMIX WITH OTHER INTRAVENOUS SOLUTIONS. (SEE WARNINGS SECTION.)

Administer by DEEP INTRAMUSCULAR INJECTION in the upper, outer quadrant of the buttock (dorsogluteal) or the ventrogluteal site. In neonates, infants and small children, the midlateral aspect of the thigh may be preferable. Administration in the anterolateral thigh is not recommended due to the adverse effects observed (see WARNINGS section), and vascularity of this region. When doses are repeated, vary the injection site.

Because of the high concentration of suspended material in this product, the needle may be blocked if the injection is not made at a slow, steady rate.

Parenteral drug products should be inspected visually for particulate matter and discoloration prior to administration whenever solution and container permit.

HOW SUPPLIED

Bicillin L-A (penicillin G benzathine injectable suspension) is supplied in packages of 10 disposable syringes as follows:

1 mL size, containing 600,000 units per syringe, (21 gauge, thin-wall 1-inch needle for pediatric use), with 0.11 mEq of sodium per 600,000 units of penicillin G (2.59 mg of sodium per 600,000 units of penicillin G), NDC 60793-700-10.

2 mL size, containing 1,200,000 units per syringe, (21 gauge, thin-wall 1-1/2-inch needle), with 0.22 mEq of sodium per 1,200,000 units of penicillin G (5.17 mg of sodium per 1,200,000 units of penicillin G), NDC 60793-701-10.

4 mL size, containing 2,400,000 units per syringe (18 gauge, × 1–1/2-inch needle), with 0.45 mEq of sodium per 2,400,000 units of penicillin G (10.32 mg of sodium per 2,400,000 units of penicillin G), NDC 60793-702-10.

STORAGE AND HANDLING

Store in a refrigerator, 2° to 8°C (36° to 46°F).

Keep from freezing.

REFERENCES

1. SHAW, E.: Transverse myelitis from injection of penicillin. Am. J. Dis. Child., 111:548, 1966.
2. KNOWLES, J.: Accidental intra-arterial injection of penicillin. Am. J. Dis. Child., 111:552, 1966.
3. DARBY, C. et al: Ischemia following an intragluteal injection of benzathine-procaine penicillin G mixture in a one-year-old boy. Clin. Pediatrics, 12:485, 1973.
4. BROWN, L. & NELSON, A.: Postinfectious intravascular thrombosis with gangrene. Arch. Surg., 94:652, 1967.
5. BORENSTINE, J.: Transverse myelitis and penicillin (Correspondence). Am. J. Dis. Child., 112:166, 1966.
6. ATKINSON, J.: Transverse myelopathy secondary to penicillin injection. J. Pediatrics, 75:867, 1969.
7. TALBERT, J. et al: Gangrene of the foot following intramuscular injection in the lateral thigh: A case report with recommendations for prevention. J. Pediatrics, 70:110, 1967.
8. FISHER, T.: Medicolegal affairs. Canad. Med. Assoc. J., 112:395, 1975.
9. SCHANZER, H. et al: Accidental intra-arterial injection of penicillin G. JAMA, 242:1289, 1979.

LAB-0588-20.0
Revised: 09/2023

PRINCIPAL DISPLAY PANEL - 1 mL Syringe Label

NDC 60793-700-01

BICILLIN® L-A
(penicillin G benzathine injectable suspension)
600,000 units per 1 mL

FOR DEEP INTRAMUSCULAR
INJECTION ONLY
WARNING: FATAL IF
GIVEN BY OTHER ROUTES

Distributed by
Pfizer Inc
New York, NY 10017

PRINCIPAL DISPLAY PANEL - 1 mL Syringe Package

NDC 60793-700-10
Contains 10 of NDC 60793-700-01

Ten Syringes (1 mL size)

Bicillin® L-A
(penicillin G benzathine injectable suspension)

600,000 units per 1 mL

FOR PEDIATRIC USE

FOR DEEP INTRAMUSCULAR INJECTION ONLY

WARNING: FATAL IF GIVEN BY OTHER ROUTES
BEFORE INJECTING, SEE PACKAGE INSERT FOR ADMINISTRATION INSTRUCTIONS.

Pfizer Hospital

Rx only

PRINCIPAL DISPLAY PANEL - 2 mL Syringe Label

NDC 60793-701-02

BICILLIN® L-A
(penicillin G benzathine injectable suspension)
1,200,000 units per 2 mL

FOR DEEP INTRAMUSCULAR
INJECTION ONLY
WARNING: FATAL IF
GIVEN BY OTHER ROUTES

Distributed by
Pfizer Inc
New York, NY 10017

PRINCIPAL DISPLAY PANEL - 2 mL Syringe Package

NDC 60793-701-10
Contains 10 of NDC 60793-701-02

Ten Syringes (2 mL size)

Bicillin® L-A
(penicillin G benzathine injectable suspension)

1,200,000 units per 2 mL

FOR DEEP INTRAMUSCULAR INJECTION ONLY

WARNING: FATAL IF GIVEN BY OTHER ROUTES
BEFORE INJECTING, SEE PACKAGE INSERT FOR ADMINISTRATION INSTRUCTIONS.

Pfizer Hospital

Rx only

PRINCIPAL DISPLAY PANEL - 4 mL Syringe Label

NDC 60793-702-04

BICILLIN® L-A
(penicillin G benzathine
injectable suspension)
2,400,000 units per 4 mL

FOR DEEP INTRAMUSCULAR
INJECTION ONLY

WARNING: FATAL IF
GIVEN BY OTHER ROUTES

Distributed by
Pfizer Inc
New York, NY 10017

PRINCIPAL DISPLAY PANEL - 4 mL Syringe Package

NDC 60793-702-10
Contains 10 of NDC 60793-702-04

Ten Syringes (4 mL size)

Bicillin® L-A
(penicillin G benzathine injectable suspension)

2,400,000 units per 4 mL

disposable syringe

FOR DEEP INTRAMUSCULAR INJECTION ONLY

WARNING: FATAL IF GIVEN BY OTHER ROUTES
BEFORE INJECTING, SEE PACKAGE INSERT FOR ADMINISTRATION INSTRUCTIONS.

Pfizer Hospital

Rx only